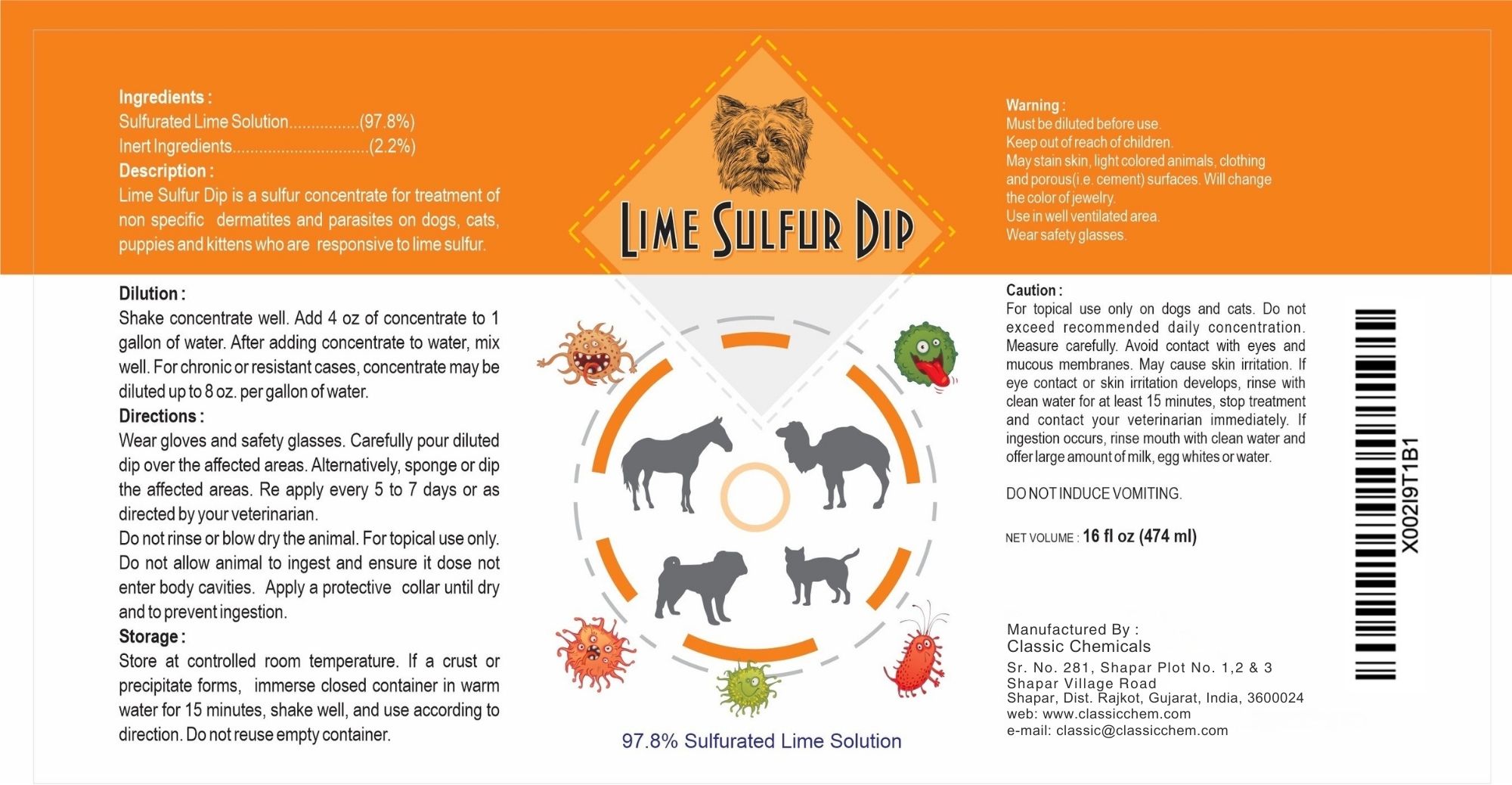 DRUG LABEL: LIME SULFUR DIP
NDC: 86235-100 | Form: LIQUID
Manufacturer: CLASSIC CHEMICALS
Category: animal | Type: OTC ANIMAL DRUG LABEL
Date: 20250710

ACTIVE INGREDIENTS: CALCIUM POLYSULFIDE 25 g/100 mL
INACTIVE INGREDIENTS: WATER

Ingredients:
Sulfurated Lime Solution…..(97.8%)
Inert Ingredients…..2.2%

Description:
Lime Sulfur Dip is a sulfur concentrate for treatment of non specific dermatitis and parasites on dogs, cats, puppies and kittens who are responsive to lime sulfur.

Dilution:
Shake concentrate well. Add 4 oz of concentrate to 1 gallon of water. After adding concentrate to water, mix well. For chronic or resistant cases, concentrate may be diluted up to 8 oz. per gallon of water.

Directions
Wear gloves and safety glasses. Carefully pour diluted dip over the affected areas. Alternatively, sponge or dip the affected areas. Re apply every 5 to 7 days or as directed by your veterinarian.
Do not rinse or blow dry the animal. For topic use only. Do not allow animal to ingest and ensure it does not enter body cavities. Apply a protective collar until dry and to prevent ingestion.

Storage:
Store at controlled room temperature. If a crust or precipitate forms, immerse closed container in warm water for 15 minutes, shake well, and use according to direction. Do not reuse empty container.

Warning:
Must be diluted before use.
Keep out of reach of children.
May stain skin, light colored animals, clothing and porous (i.e. cement) surfaces. Will change the color of jewelry.
Use in well ventilated area.
Wear safety glasses.

Caution:
For topical use only on dogs and cats. Do not exceed recommended daily concentration. Measure carefully. Avoid contact with eyes and mucous membranes. May cause skin irritation. If eye contact or skin irritation develops, rinse with clean water for at least 15 minutes, stop treatment and contact your veterinarian immediately. If ingestion occurs, rinse mouth with clean water and offer large amount of milk, egg whites or water.

DO NOT INDUCE VOMITING